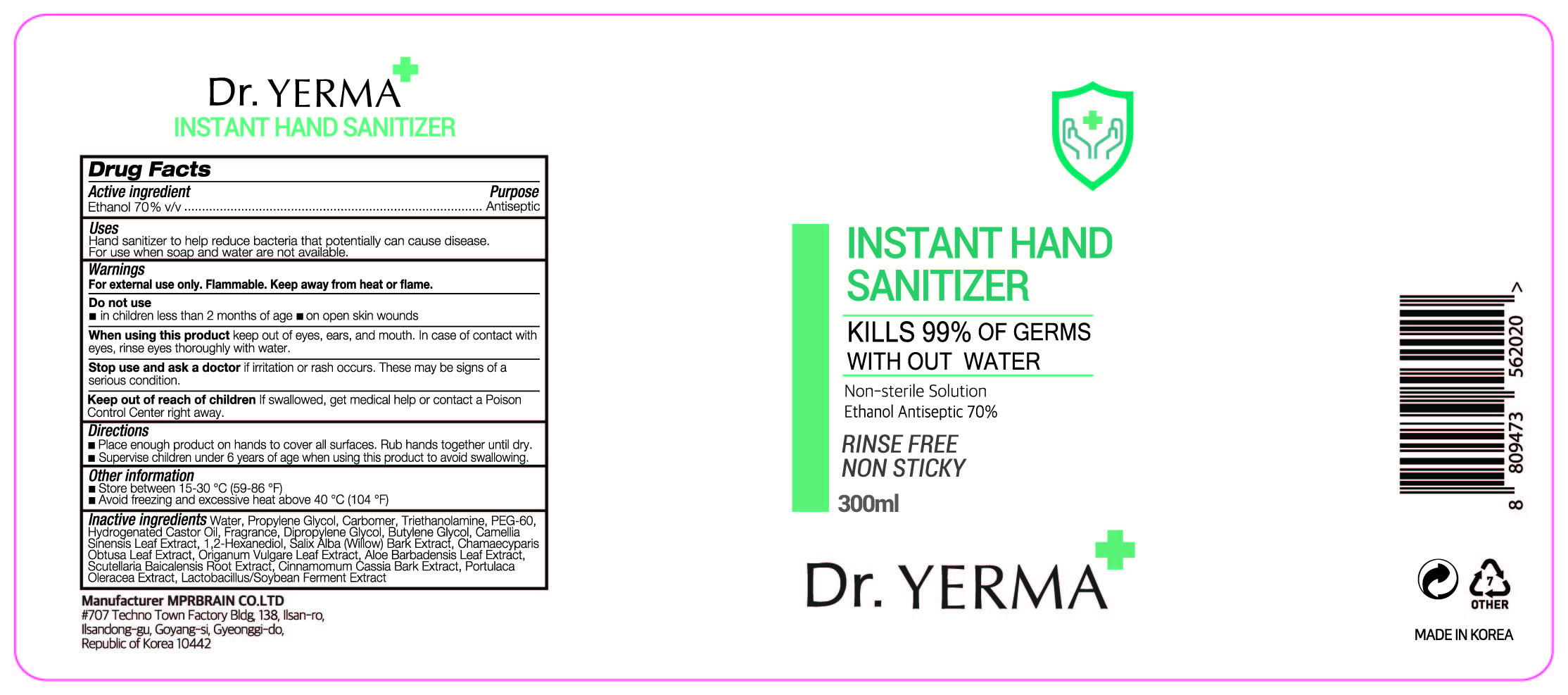 DRUG LABEL: Dr. YERMA INSTANT HAND SANITIZER
NDC: 74741-7302 | Form: GEL
Manufacturer: MPRBRAIN CO.LTD
Category: otc | Type: HUMAN OTC DRUG LABEL
Date: 20200612

ACTIVE INGREDIENTS: ALCOHOL 210 mL/300 mL
INACTIVE INGREDIENTS: SOYBEAN GERM; DIPROPYLENE GLYCOL; CARBOMER HOMOPOLYMER, UNSPECIFIED TYPE; GREEN TEA LEAF; PEG-60 HYDROGENATED CASTOR OIL; BUTYLENE GLYCOL; WATER; PROPYLENE GLYCOL; SCUTELLARIA BAICALENSIS ROOT; CHINESE CINNAMON; PURSLANE; TROLAMINE; ALOE VERA LEAF; OREGANO; SALIX ALBA BARK; CHAMAECYPARIS OBTUSA LEAF; 1,2-HEXANEDIOL

Dr. YERMA INSTANT HAND SANITIZER 300 ml : 74741-7302-1 (Bottle)